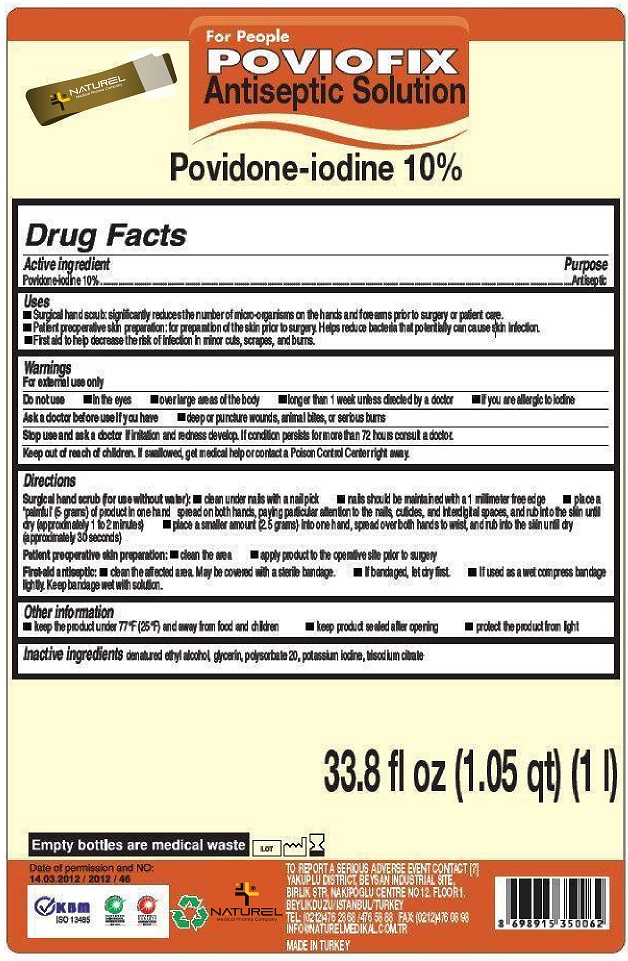 DRUG LABEL: POVIOFIX Antiseptic
NDC: 69249-000 | Form: SOLUTION
Manufacturer: NATUREL MEDIKAL ILAC SANAYI VE TICARET LIMITED SIRKETI
Category: otc | Type: HUMAN OTC DRUG LABEL
Date: 20231221

ACTIVE INGREDIENTS: POVIDONE-IODINE 100 mg/1 mL
INACTIVE INGREDIENTS: ALCOHOL; GLYCERIN; POLYSORBATE 20; SODIUM CITRATE

POVIOFIX Antiseptic

Active ingredient

Povidone-iodine 10%

Purpose

Antiseptic

Uses

- Surgical hand scrub: significantly reduces the number of micro-organisms on the hands and forearms prior to surgery or patient care.
- Patient preoperative skin preparation: for preparation of the skin prior to surgery. Helps reduce bacteria that potentially can cause skin infection.
- First aid to help decrease the risk of infection in minor cuts, scrapes, and burns.

Warnings

For external use only

Do not use

- in the eyes - over large areas of the body - longer than 1 week unless directed by a doctor - if you are allergic to iodine

Ask a doctor before use if you have

deep or puncture wounds, animal bites, or serious burns

Stop use and ask a doctor if

irritation and redness develop. If condition persists for more than 72 hours consult a doctor.

Keep out of reach of children.

If swallowed, get medical help or contact a Poison Control Center right away.

Directions

Surgical hand scrub (for use without water):

Patient preoperative skin preparation:

First-aid antiseptic:

- clean under nails with a nail pick
- nails should be maintained with a 1 millimeter free edge
- place a ‘palmful’ (5 grams) of product in one hand spread on both hands, paying particular attention to the nails, cuticles, and interdigital spaces, and rub into the skin until dry (approximately 1 to 2 minutes)
- place a smaller amount (2.5 grams) into one hand, spread over both hands to wrist, and rub into the skin until dry (approximately 30 seconds)

- clean the area
- apply product to the operative site prior to surgery

- clean the affected area. May be covered with a sterile bandage.
- If bandaged, let dry first.
- If used as a wet compress bandage lightly. Keep bandage wet with solution.

Other information

- keep the product under 77°F (25°F) and away from food and children
- keep product sealed after opening

Inactive ingredients

denatured ethyl alcohol, glycerin, polysorbate 20, potassium iodine, trisodium citrate

TO REPORT A SERIOUS ADVERSE EVENT CONTACT [?] YAKUPLU DISTRICT, BEYSAN INDUSTRIAL SITE, BIRLIK STR, NAKIPOGLU CENTRE NO 12. FLOOR 1. BEYLIKDUZU/ISTANBUL/TURKEY TEL: (0212)476 28 68 /476 58 88 FAX: (0212)476 08 98 INFO@NATURELMEDIKAL.COM.TR MADE IN TURKEY

PACKAGE LABEL

NATUREL For People POVIOFIX Antiseptic Solution Povidone-iodine 10% 33.8 fl oz (1.05 qt) (1 l)